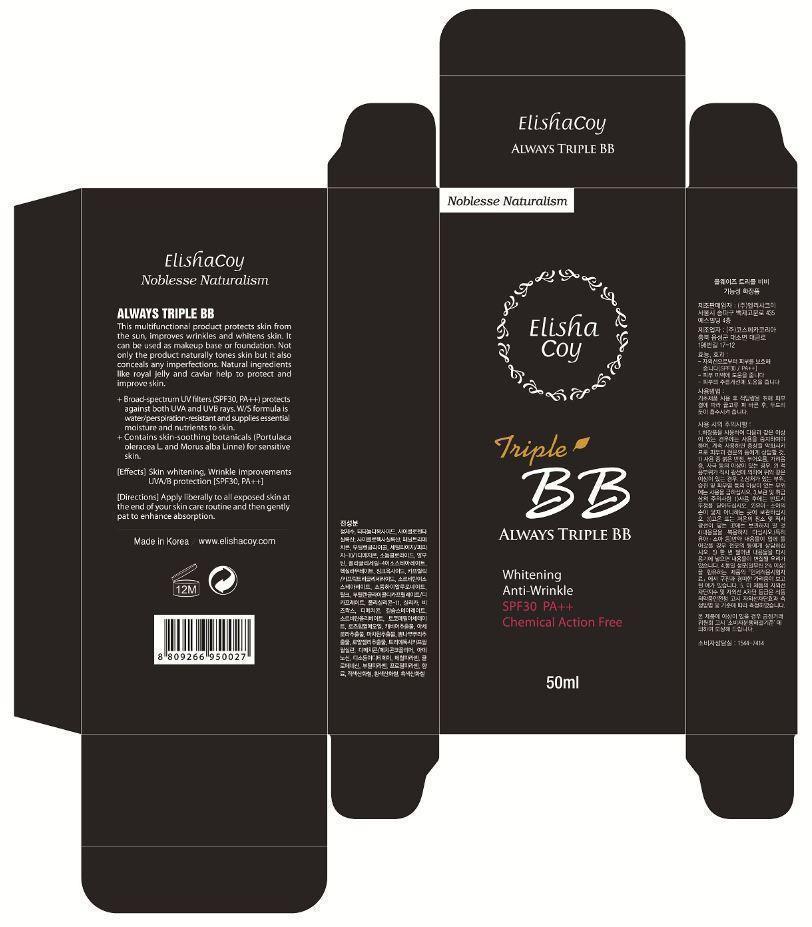 DRUG LABEL: Always Triple BB
NDC: 53727-101 | Form: CREAM
Manufacturer: Cosmecca Korea Co., Ltd.
Category: otc | Type: HUMAN OTC DRUG LABEL
Date: 20140819

ACTIVE INGREDIENTS: TITANIUM DIOXIDE 5 g/50 g; ZINC OXIDE 0.5 g/50 g
INACTIVE INGREDIENTS: WATER; PHENYL TRIMETHICONE; DIMETHICONE; CYCLOMETHICONE; PROPYLENE GLYCOL DICAPRYLATE/DICAPRATE; BUTYLENE GLYCOL; CYCLOMETHICONE 5; PROPYLENE GLYCOL; SILICON DIOXIDE; BIS-PEG/PPG-16/16 PEG/PPG-16/16 DIMETHICONE; BUTYLENE GLYCOL DICAPRYLATE/DICAPRATE; ARBUTIN; SODIUM CHLORIDE; SORBITAN SESQUIOLEATE; TRIETHOXYCAPRYLYLSILANE; DISTEARDIMONIUM HECTORITE; TALC; GLYCERIN; CAVIAR, UNSPECIFIED; ROYAL JELLY; MALPIGHIA GLABRA FRUIT; CERESIN; ROSA CANINA FRUIT OIL; DIMETHICONE/VINYL DIMETHICONE CROSSPOLYMER (HARD PARTICLE); PROPYLENE CARBONATE; METHYLPARABEN; CHLORPHENESIN; HEXYL LAURATE; BUTYLPARABEN; PROPYLPARABEN; .ALPHA.-TOCOPHEROL ACETATE; DIMETHICONE/DIENE DIMETHICONE CROSSPOLYMER; ADENOSINE; EDETATE DISODIUM; BUTYLATED HYDROXYTOLUENE; HYALURONATE SODIUM; FERRIC OXIDE RED

ACTIVE INGREDIENT

Titanium Dioxide (10.4%), Zinc Oxide (1.44%)

PURPOSE

Whitening

Anti-Wrinkle

SPF30 PA++

Chemical Action Free

Keep out of reach of children.

INDICATIONS AND USAGE

ElishaCoy

Noblesse Naturalism

Always Triple BB

This multifunctional product protects skin from the sun, improves wrinkles and whitens skin. It can be used as makeup base or foundation. Not only the product naturally tones skin but it also conceals any imperfections. Natural ingredients like royal jelly and caviar help to protect and improve skin.

+ Broad-Spectrum UV filters (SPF30, PA++) protects against both UVA and UVB rays. W/S formula is water/perspiration-resistant and supplies essential moisture and nutrients to skin.

+ Contains skin-soothing botanicals (Portulaca oleracea L. and Morus alba Linne) for sensitive skin.

[Effects] Skin whitening, Wrinkle improvements

UVA/B Protection [SPF30, PA++]

Warnings

DOSAGE AND ADMINISTRATION

[Directions] Apply liberally to all exposed skin at the end of your skin care routine and then gently pat to enhance absorption.

INACTIVE INGREDIENT

Water, Phenyl Trimethicone, Dimethicone, Cyclomethicone, Propylene Glycol Dicaprylata/Dicaprate, Butylene Glycol, Cyclopentasiloxane, Propylene Glycol, Silica, Bis-PEG/PPG-14/14 Dimethicone, Butylene Glycol Dicaprylate/Dicaprate, Arbutin, Sodium Chloride, Sorbitan Sesquioleate, Triethoxycaprylylsilane, Disteardimonium Hectorite, Talc, Glycerin, Caviar Extract, Royal Jelly Extract, Malpighia Punicifolia (Acerola) Fruit Extract, Ozokerite, Rosa Canina Fruit Oil, Dimethicone/Vinyl Dimethicone Crosspolymer, Propylene Carbonate, Methylparaben, Chlorphenesin, Hexyl Laurate, Butylparaben, Propylparaben, Tocopheryl Acetate, Dimethicone/Methicone Copolymer, Adenosine, Disodium EDTA, BHT, Sodium Hyaluronate, Iron Oxides